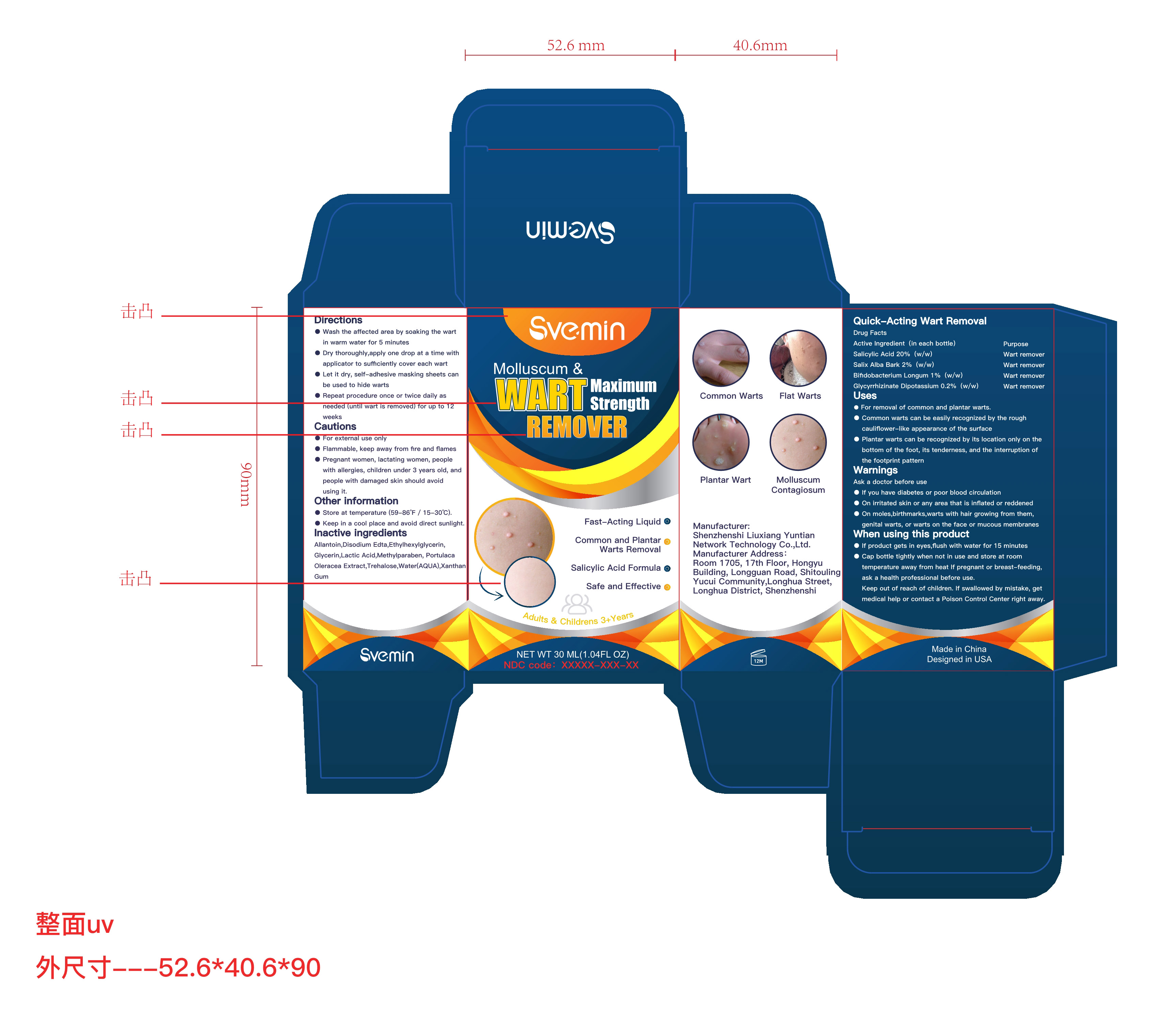 DRUG LABEL: Quick-Acting Wart Removal
NDC: 83575-001 | Form: LIQUID
Manufacturer: Shenzhenshi Liuxiang Yuntian Network Technology Co., Ltd.
Category: otc | Type: HUMAN OTC DRUG LABEL
Date: 20230711

ACTIVE INGREDIENTS: GLYCYRRHIZINATE DIPOTASSIUM 0.2 mg/100 mL; SALIX ALBA BARK 2 mg/100 mL; SALICYLIC ACID 20 mg/100 mL; BIFIDOBACTERIUM LONGUM 1 mg/100 mL
INACTIVE INGREDIENTS: EDETATE DISODIUM ANHYDROUS; GLYCERIN; XANTHAN GUM; LACTIC ACID; PURSLANE; WATER; ALLANTOIN; METHYLPARABEN; TREHALOSE; ETHYLHEXYLGLYCERIN

ACTIVE INGREDIENT

Salicylic Acid 20%

Salix Alba Bark 2%

Bifidobacterium Longum 1%

Glycyrrhizinate Dipotassium 0.2%

Purpose

Wart remover

Uses

- For removal of common and plantar warts.
- Common warts can be easily recognized by the rough cauliflflower-like appearance of the surface
- Plantar warts can be recognized by its location only on the bottom of the foot, its tenderness, and the interruption of the footprint pattern

Warnings

- If you have diabetes or poor blood circulation
- On irritated skin or any area that is inflflated or reddened
- On moles,birthmarks,warts with hair growing from them, genital warts, or warts on the face or mucous membranes

DO NOT USE

Cautions
- For external use only
- Flammable, keep away from fire and flames
- Pregnant women, lactating women, people with allergies, children under 3 years old, and people with damaged skin should avoid using it

When using this product

- If product gets in eyes,flush with water for 15 minutes
- Cap bottle tightly when not in use and store at room temperature away from heat If pregnant or breast-feeding, ask a health professional before use.
Keep out of reach of children. If swallowed by mistake, get medical help or contact a Poison Control Center right away.

STOP USE

If swallowed by mistake, get medical help or contact a Poison Control Center right away.

Keep out of reach of children.

Directions

-Wash the affffected area by soaking the wart in warm water for 5 minutes
- Dry thoroughly,apply one drop at a time with applicator to suffiffifficiently cover each wart
- Let it dry, self-adhesive masking sheets can be used to hide warts
- Repeat procedure once or twice daily as needed (until wart is removed) for up to 12 weeks

Other information

- Store at temperature (59-86℉ / 15-30℃).
- Keep in a cool place and avoid direct sunlight.

INACTIVE INGREDIENT

Allantoin,Disodium Edta,Ethylhexylglycerin, Glycerin,Lactic Acid,Methylparaben, Portulaca Oleracea Extract,Trehalose,Water(AQUA),Xanthan Gum